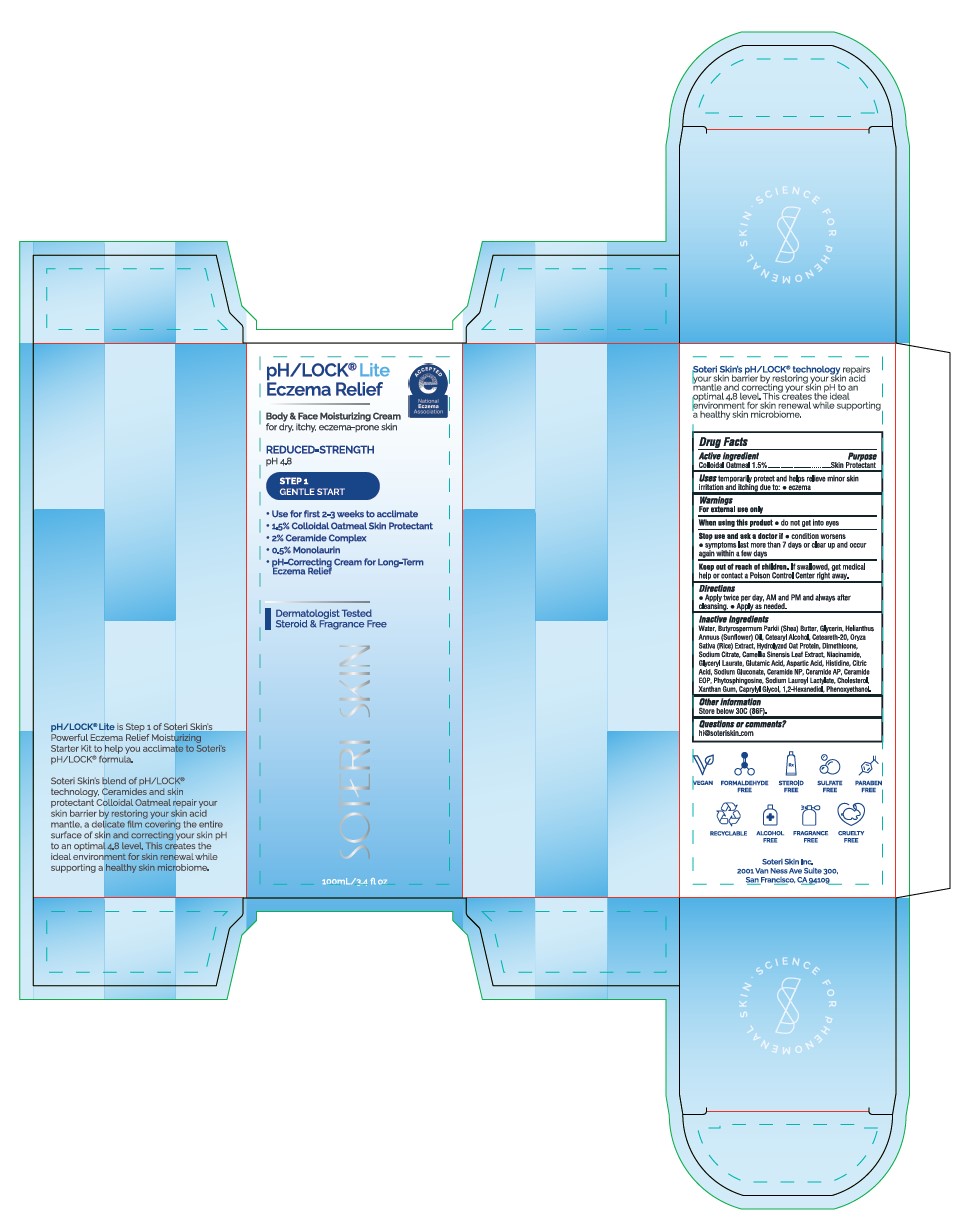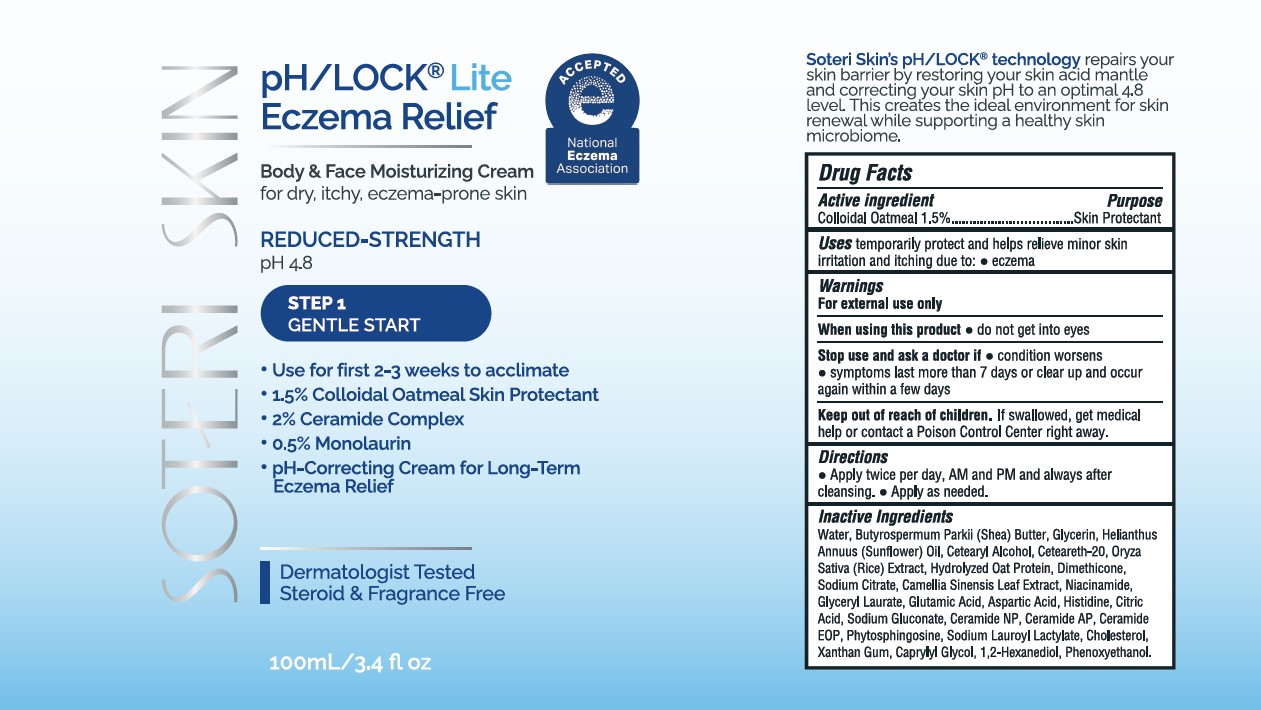 DRUG LABEL: pH/Lock Lite Eczema Relief Gentle Start
NDC: 85265-101 | Form: EMULSION
Manufacturer: Soteri Skin, Inc.
Category: otc | Type: HUMAN OTC DRUG LABEL
Date: 20250325

ACTIVE INGREDIENTS: OATMEAL 1.5 g/100 mL
INACTIVE INGREDIENTS: GLYCERIN; NIACINAMIDE; GLUTAMIC ACID; BUTYROSPERMUM PARKII (SHEA) BUTTER; PHENOXYETHANOL; CERAMIDE AP; GLYCERYL LAURATE; WATER; CERAMIDE 1; CHOLESTEROL; CITRIC ACID; SODIUM LAUROYL LACTYLATE; 1,2-HEXANEDIOL; CETEARYL ALCOHOL; RICE GERM; HISTIDINE; SODIUM GLUCONATE; HELIANTHUS ANNUUS (SUNFLOWER) SEED OIL; CETEARETH-20; PHYTOSPHINGOSINE; XANTHAN GUM; OAT; DIMETHICONE; SODIUM CITRATE; TEA LEAF; ASPARTIC ACID; CERAMIDE NP; CAPRYLYL GLYCOL

Soteri Skin pH/Lock Eczema Relief Gentle Start

Active Ingredient

Colloidal Oatmeal 1.5%

Purpose

Skin Protectant

Uses

temporarily protect and helps relieve minor skin irritation and itching due to:

- eczema

Warnings

For external use only

When using this product

- do not get into eyes

Stop use and ask doctor if

- condition worsens
- symptoms last more than 7 days or clear up and occur again within a few days

Uses - Keep out of reach of children

Keep out of reach of children. If swallowed, get medical help or contact a Poison Control Center right away.

Directions

- Apply twice per day, AM and PM and always after cleansing.
- Apply as needed.

Inactive Ingredients

Water, Butyrospermum Parkii (Shea) Butter, Glycerin, Helianthus Annuus (Sunflower) Oil, Cetearyl Alcohol, Ceteareth-20, Oryza Sativa (Rice) Extract, Hydrolyzed Oat Protein, Dimethicone, Sodium Citrate, Camellia Sinensis Leaf Extract, Niacinamide, Glyceryl Laurate, Glutamic Acid, Aspartic Acid, Histidine, Citric Acid, Sodium Gluconate, Ceramide NP, Ceramide AP, Ceramide EOP, Phytosphingosine, Sodium Lauroyl Lactylate, Cholesterol, Xanthan Gum, Caprylyl Glycol, 1,2-Hexanediol, Phenoxyethanol.

Other Information

Store below 30C (86F)